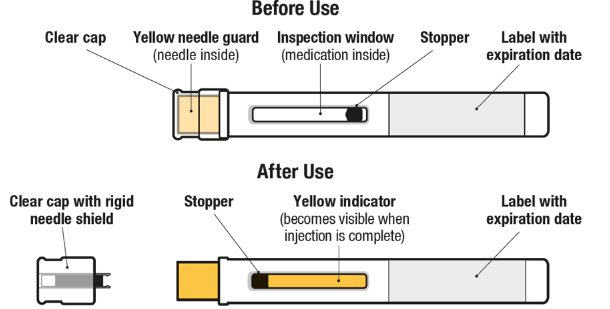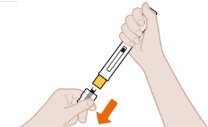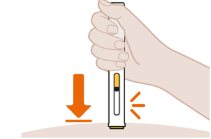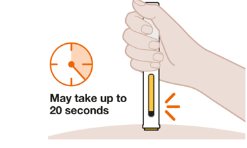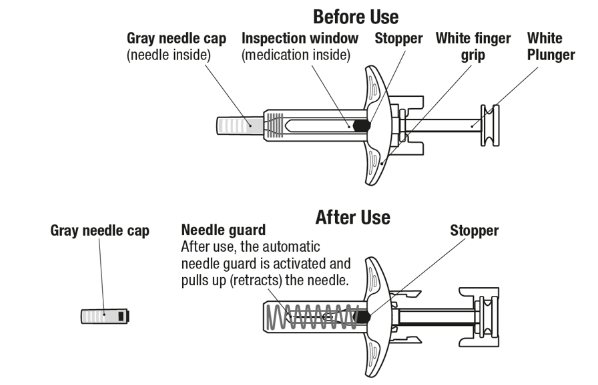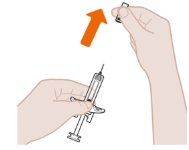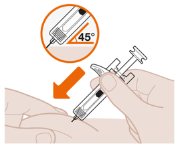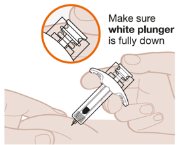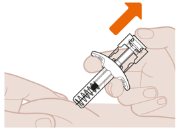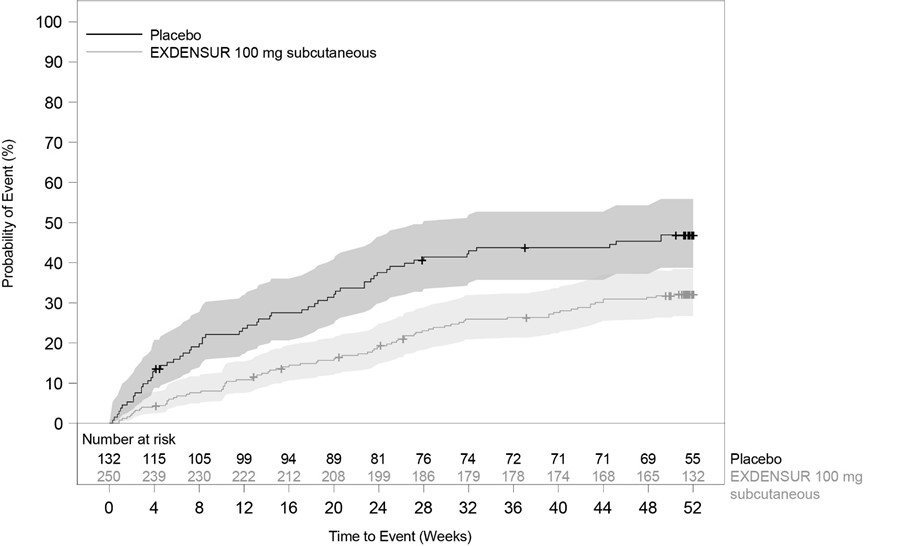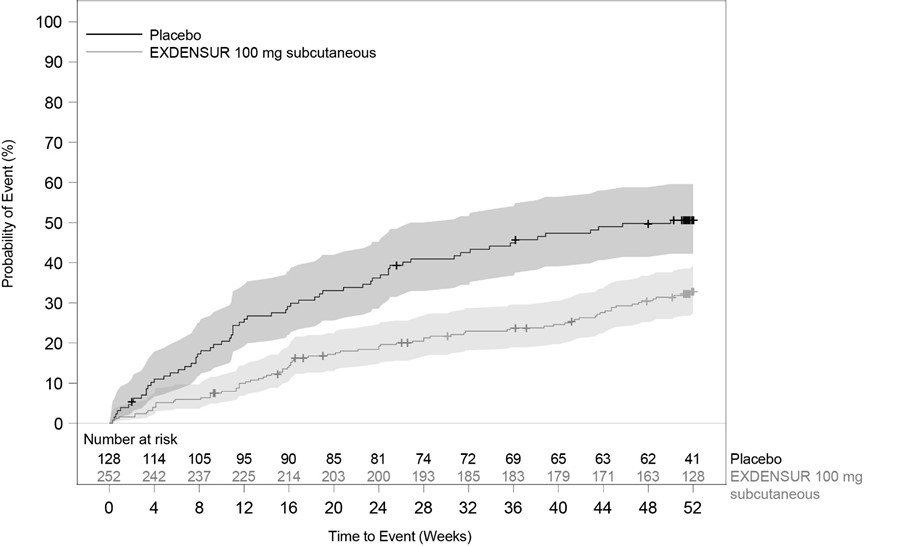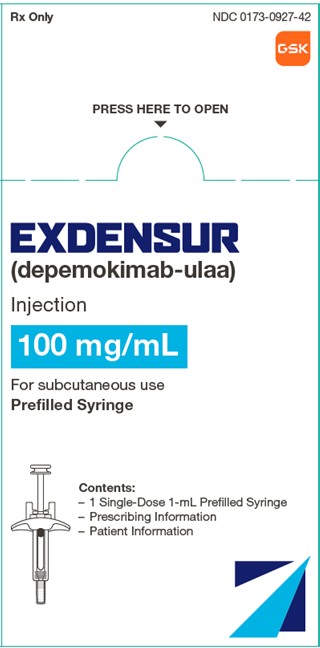 DRUG LABEL: Exdensur
NDC: 0173-0927 | Form: INJECTION, SOLUTION
Manufacturer: GlaxoSmithKline LLC
Category: prescription | Type: HUMAN PRESCRIPTION DRUG LABEL
Date: 20251216

ACTIVE INGREDIENTS: DEPEMOKIMAB 100 mg/1 mL
INACTIVE INGREDIENTS: ARGININE HYDROCHLORIDE; EDETATE DISODIUM; HISTIDINE; HISTIDINE HYDROCHLORIDE; POLYSORBATE 80; TREHALOSE DIHYDRATE

HIGHLIGHTS OF PRESCRIBING INFORMATION

These highlights do not include all the information needed to use EXDENSUR safely and effectively. See full prescribing information for EXDENSUR.
EXDENSUR (depemokimab-ulaa) injection, for subcutaneous use
Initial U.S. Approval: 2025

1 INDICATIONS AND USAGE

EXDENSUR is an interleukin‑5 (IL-5) antagonist, a monoclonal antibody (humanized immunoglobulin G [IgG]1 kappa) indicated for add-on maintenance treatment of severe asthma characterized by an eosinophilic phenotype in adult and pediatric patients aged 12 years and older. (1)

Limitations of Use: Not for relief of acute bronchospasm or status asthmaticus. (1)

2 DOSAGE AND ADMINISTRATION

The recommended dosage is 100 mg administered once every 6 months by subcutaneous (SC) injection into the upper arm, thigh, or abdomen. (2.1)

- EXDENSUR should be administered by a healthcare provider. (2.2)
- See full prescribing information for preparation and administration instructions. (2.2)

3 DOSAGE FORMS AND STRENGTHS

Injection:

- 100 mg/mL solution in a single-dose, prefilled pen (3)
- 100 mg/mL solution in a single-dose, prefilled syringe with needle guard (3)

4 CONTRAINDICATIONS

None. (4)

5 WARNINGS AND PRECAUTIONS

- Hypersensitivity reactions, including anaphylaxis, can occur after administration of EXDENSUR. If a hypersensitivity reaction occurs, discontinue EXDENSUR and initiate appropriate therapy. (5.1)
- Do not abruptly discontinue systemic or inhaled corticosteroids upon initiation of therapy with EXDENSUR. Reduce corticosteroid dose gradually, if appropriate. (5.3)
- Treat pre-existing helminth infections before initiating therapy with EXDENSUR. If patients become infected while receiving treatment with EXDENSUR and do not respond to anti‑helminth treatment, discontinue EXDENSUR until the parasitic infection resolves. (5.4)

6 ADVERSE REACTIONS

The most common adverse reactions (incidence ≥4%) are upper respiratory tract infection, allergic rhinitis, influenza, arthralgia, and pharyngitis. (6.1)

To report SUSPECTED ADVERSE REACTIONS, contact GlaxoSmithKline at 1-888-825-5249 or FDA at 1-800-FDA-1088 or www.fda.gov/medwatch.

8 USE IN SPECIFIC POPULATIONS

Pregnancy: EXDENSUR can cross the placenta during pregnancy and the presence of the YTE modification may prolong and increase exposure to the infant exposed in utero. The impact of EXDENSUR transmission to the fetus should be considered. (8.1)

FULL PRESCRIBING INFORMATION

1 INDICATIONS AND USAGE

EXDENSUR is indicated for the add‑on maintenance treatment of severe asthma characterized by an eosinophilic phenotype in adult and pediatric patients aged 12 years and older.

Limitations of Use

EXDENSUR is not indicated for the relief of acute bronchospasm or status asthmaticus [see Warnings and Precautions (5.2)].

2 DOSAGE AND ADMINISTRATION

2.1 Recommended Dosage

The recommended dosage is 100 mg once every 6 months administered by subcutaneous (SC) injection into the upper arm, thigh, or abdomen avoiding 2 inches (5 cm) around the navel [see Dosage and Administration (2.2)].

Missed Dose(s)

If a dose is missed, administer the missed dose as soon as possible and resume the once every 6‑month injection schedule from the date of when the missed dose was given.

2.2 Preparation and Administration Instructions for EXDENSUR

- EXDENSUR is for subcutaneous (SC) use only.
- EXDENSUR should be administered by a healthcare provider.
  Do not use EXDENSUR prefilled pen or syringe if the security seal on the carton has been broken.
  Do not use EXDENSUR prefilled pen or syringe if it has been dropped or damaged.

Preparation Instructions

1. Remove the prefilled pen or prefilled syringe from the refrigerator. Holding the middle of the prefilled pen or prefilled syringe, take it out from the tray and allow it to sit at room temperature for 30 minutes prior to injection. Do not warm EXDENSUR injection in any other way. Do not remove the needle cap until you are ready to inject. Do not use the pen or syringe if it has been left out of the carton for more than 8 hours.
2. Parenteral drug products should be inspected visually for particulate matter and discoloration prior to administration whenever solution and container permit. EXDENSUR should be colorless to yellow to brown, clear to opalescent in color. Do not use EXDENSUR if the product exhibits discoloration, cloudiness, or particulate matter. It is normal to see an air bubble. Do not expel the air bubble prior to administration. Do not shake the device.
3. Choose the Injection Site
  Administer the injection into upper arm, thigh, or abdomen, avoiding the 2 inches (5 cm) around the navel.
  Do not give injections into areas where the skin is tender, bruised, red, or hard.

Administration Instructions for Single‑Dose Prefilled Pen

Figure 1. EXDENSUR Prefilled Pen Components

1. Pull Off the Clear Cap

Remove the clear cap by pulling it straight off, away from the yellow needle guard.

Do not press the yellow needle guard.

Do not put the cap back on the pen. This could accidentally start the injection.

Inject within 5 minutes after removing the clear cap.

2. Position the Pen at the Injection Site and Press Firmly to Start the Injection

Place the yellow needle guard flat against the skin (at a 90 degree angle to the skin).

Make sure you can see the inspection window.

The yellow needle guard will slide up into the pen.

You may hear a “click” that tells you the injection has started.

Do not use the pen if the yellow needle guard does not slide up into the pen.

3. Continue to Hold Down

Keep the pen held down against the skin. Do not lift or move the pen during the injection.

The yellow indicator will move down through the inspection window during the injection.

The injection is done when you hear the second click. Injection may take up to 20 seconds.

If you do not hear the second click, check that:

- The inspection window is filled with the yellow indicator.
- The black stopper has stopped moving.

4. Lift Pen After Injection Completes
5. Throw Away

Dispose of used pen and clear cap according to local health and safety laws.

Administration Instructions for Single‑Dose Prefilled Syringe

Figure 2. EXDENSUR Prefilled Syringe Components

1. Pull Off the Gray Needle Cap

Remove the gray needle cap from the syringe by pulling it straight off, away from the needle.

Do not handle the syringe by the white plunger while removing the gray needle cap.

Do not put the gray needle cap back onto the syringe.

Inject within 5 minutes after removing the gray needle cap.

2. Position the Syringe at the Injection Site

Use your free hand to gently pinch the skin around the cleaned injection site.

Do not handle the syringe by the white plunger while inserting the needle into the pinched skin.

Hold the middle of the syringe and insert the entire needle into the pinched skin at a 45 degree angle, as shown.

3. Start the Injection and Fully Press the White Plunger

Slowly push down on the white plunger with your thumb to inject the full dose.

Make sure the white plunger is pushed all the way down until the stopper reaches the bottom of the syringe and all of the medication is injected.

4. Slowly Lift Thumb After Injection Completes

Slowly lift your thumb up. This will allow the white plunger to come up and the needle to automatically pull up (retract) into the needle guard.

After removing the syringe from the injection site, release the pinched skin.

5. Throw Away

Dispose of used syringe according to local health and safety laws.

3 DOSAGE FORMS AND STRENGTHS

Injection: a colorless, yellow to brown, clear to opalescent solution available as:

- 100 mg/mL solution in a single‑dose, prefilled pen
- 100 mg/mL solution in a single‑dose, prefilled syringe with needle guard

4 CONTRAINDICATIONS

None.

5 WARNINGS AND PRECAUTIONS

5.1 Hypersensitivity Reactions

Hypersensitivity reactions, including anaphylaxis, can occur following administration of EXDENSUR. If a hypersensitivity reaction occurs, discontinue EXDENSUR and initiate appropriate therapy.

5.2 Acute Asthma Symptoms or Deteriorating Disease

EXDENSUR should not be used to treat acute asthma symptoms or acute exacerbations. Do not use EXDENSUR to treat acute bronchospasm or status asthmaticus. Patients should seek medical advice if their asthma remains uncontrolled or worsens after initiation of treatment with EXDENSUR.

5.3 Risk Associated with Abrupt Reduction of Corticosteroid Dosage

Reduction in corticosteroid dose may be associated with systemic withdrawal symptoms and/or unmask conditions previously suppressed by systemic corticosteroid therapy. Do not abruptly discontinue systemic or inhaled corticosteroids upon initiation of EXDENSUR therapy. Reductions in corticosteroid dose, if appropriate, should be gradual and performed under the supervision of a healthcare provider.

5.4 Parasitic (Helminth) Infection

Eosinophils may be involved in the immunological response to some helminth infections. Patients with pre‑existing helminth infections were excluded from participation in the clinical trials. It is unknown if EXDENSUR will influence a patient’s response against parasitic infections. Patients with pre‑existing helminth infections should be treated for their infection prior to initiation of EXDENSUR therapy. If patients become infected while receiving treatment with EXDENSUR and do not respond to anti‑helminth treatment, discontinue treatment with EXDENSUR until the infection resolves.

6 ADVERSE REACTIONS

The following adverse reactions are discussed in greater detail in other sections of the labeling:

- Hypersensitivity Reactions [see Warnings and Precautions (5.1)].

6.1 Clinical Trials Experience

Because clinical trials are conducted under widely varying conditions, adverse reaction rates observed in the clinical trials of a drug cannot be directly compared with rates in the clinical trials of another drug and may not reflect the rates observed in practice.

The safety of EXDENSUR was based on a pooled safety population from 2 replicate, randomized, double‑blind, parallel‑group, placebo‑controlled, multicenter clinical trials (SWIFT‑1 and SWIFT‑2) of 52 weeks duration. The 2 trials included 762 adult and pediatric patients 12 years of age and older with asthma, who received either EXDENSUR 100 mg or placebo administered subcutaneously once every 6 months in addition to their existing background medications for asthma [see Clinical Studies (14)]. A total of 475 patients received 2 doses of EXDENSUR 100 mg in these trials.

Adverse reactions with EXDENSUR with incidence of ≥4% are shown in Table 1.

Table 1. Adverse Reactions with EXDENSUR with an Incidence ≥4% and More Common than Placebo in Patients with Asthma
Adverse Reaction | EXDENSUR; (N = 501); n (%) | Placebo; (N = 261); n (%)
Upper respiratory tract infection | 46 (9) | 20 (8)
Allergic rhinitis | 29 (6) | 7 (3)
Influenza | 24 (5) | 11 (4)
Arthralgia | 19 (4) | 8 (3)
Pharyngitis | 18 (4) | 3 (1)

Specific Adverse Reactions

Injection Site Reactions: In the pooled safety population (SWIFT‑1 and SWIFT‑2), in which EXDENSUR was administered by a healthcare provider, injection site reactions (e.g., erythema, swelling, and itching) occurred in 7 (1%) and 2 (<1%) patients receiving EXDENSUR and placebo, respectively.

8 USE IN SPECIFIC POPULATIONS

8.1 Pregnancy

Risk Summary

Available data from clinical trials with EXDENSUR use in pregnant women are insufficient to identify a drug‑associated risk of major birth defects, miscarriage, or other adverse maternal or fetal outcomes. There are risks to the mother and fetus associated with asthma in pregnancy (see Clinical Considerations).

Transport of endogenous IgG antibodies and monoclonal antibodies, such as depemokimab-ulaa, across the placenta increases as pregnancy progresses and peaks during the third trimester. The impact of the YTE modification on placental transfer is uncertain [see Clinical Pharmacology (12.1)]; however, the presence of the YTE modification may lead to prolonged and increased exposure of the infant exposed in utero, and the potential of clinical impact is unknown and should be considered. No treatment-related effects on embryofetal or postnatal development have been shown in animal studies targeting IL‑5 signaling pathways (see Data).

The background risk of major birth defects and miscarriage for the indicated population(s) is unknown. All pregnancies have a background risk of birth defect, loss, or other adverse outcomes. In the U.S. general population, the estimated background risk of major birth defects and miscarriage in clinically recognized pregnancies is 2% to 4% and 15% to 20%, respectively.

Pregnant women exposed to EXDENSUR, or their healthcare providers, should report EXDENSUR exposure by calling 1‑888‑825‑5249.

Clinical Considerations

Disease‑Associated Maternal and/or Embryofetal Risk: In women with poorly or moderately controlled asthma, evidence demonstrates that there is an increased risk of preeclampsia in the mother, and prematurity, low birth weight, and small for gestational age in the neonate. The level of asthma control should be closely monitored in pregnant women and treatment adjusted as necessary to maintain optimal control.

Data

Animal Data: Reproductive toxicology studies have not been conducted with depemokimab‑ulaa. In animal studies targeting the IL‑5 signaling pathway with a related biologic product without the YTE modification, there were no developmental effects observed [see Nonclinical Toxicology (13)]. Embryofetal development of IL‑5 deficient mice has been reported to be generally unaffected relative to wild‑type mice.

8.2 Lactation

Risk Summary

There are no data on the presence of depemokimab‑ulaa in either human or animal milk, the effects on the breastfed infant, or the effects on milk production. However, depemokimab‑ulaa is a humanized monoclonal antibody (immunoglobulin G1 [IgG1] kappa), and maternal IgG is present in human milk in small amounts. The effects of local gastrointestinal exposure and the extent of systemic exposure in the breastfed infant to EXDENSUR are unknown.

The developmental and health benefits of breastfeeding should be considered along with the mother’s clinical need for EXDENSUR, and any potential adverse effects on the breastfed child from EXDENSUR or from the underlying maternal condition.

8.4 Pediatric Use

Asthma

The safety and effectiveness of EXDENSUR for add‑on maintenance treatment of severe asthma characterized by an eosinophilic phenotype have been established in pediatric patients aged 12 years and older.

Use of EXDENSUR for this indication is supported by evidence from adequate and well‑controlled trials (SWIFT‑1 and SWIFT‑2) in adults and pediatric patients aged 12 years and older, and pharmacokinetic data in pediatric patients aged 12 years and older. A total of 30 pediatric patients aged 12 to 17 years with asthma were enrolled in the SWIFT‑1 and SWIFT‑2 trials, of whom 15 received EXDENSUR 100 mg. Pharmacokinetic and pharmacodynamic data have demonstrated no clinically significant differences in systemic exposure of depemokimab‑ulaa and reduction in blood eosinophil counts in pediatric patients aged 12 years and older compared to that observed in adults following administration of the recommended dosage of EXDENSUR. The safety of EXDENSUR in pediatric patients aged 12 years and older was generally similar to that of the adult population in SWIFT‑1 and SWIFT‑2 [see Adverse Reactions (6.1), Clinical Pharmacology (12.3), Clinical Studies (14)].

The safety and effectiveness of EXDENSUR have not been established in pediatric patients younger than 12 years of age.

8.5 Geriatric Use

Of the 501 patients with asthma treated with EXDENSUR, 133 (27%) were 65 years of age and older and 22 (4%) were 75 years of age and older. No overall differences in safety or effectiveness were observed between these patients and younger patients.

10 OVERDOSAGE

If an overdosage occurs, the patient should be treated supportively with appropriate monitoring as necessary. Consider contacting the Poison Help line (1‑800‑222‑1222) or a medical toxicologist for additional overdose management recommendations.

11 DESCRIPTION

Depemokimab‑ulaa is an interleukin‑5 (IL‑5) antagonist monoclonal antibody (humanized Immunoglobulin G1 [IgG1] kappa). Depemokimab‑ulaa is produced by recombinant DNA technology in Chinese hamster ovary cells. The estimated molecular weight of depemokimab‑ulaa is 149 kDa.

EXDENSUR (depemokimab‑ulaa) injection is a sterile, preservative‑free, colorless, yellow to brown, clear to opalescent solution for subcutaneous (SC) use.

EXDENSUR injection is supplied in a single‑dose, 1‑mL, prefilled pen with a fixed 29‑gauge, half‑inch needle or in a single‑dose, 1‑mL, prefilled syringe with a fixed 29‑gauge, half‑inch needle with a needle guard. Each 1 mL delivers 100 mg depemokimab‑ulaa, (8.43 mg) arginine HCl, (0.017 mg) edetate disodium, (1.41 mg) histidine, (2.29 mg) L‑histidine HCl monohydrate, (0.20 mg) polysorbate 80, (61.6 mg) trehalose, and Water for Injection with a pH of 6.0.

12 CLINICAL PHARMACOLOGY

12.1 Mechanism of Action

Depemokimab‑ulaa is an IL‑5 antagonist (humanized IgG1 kappa monoclonal antibody), which binds to IL‑5 with a dissociation constant of 10.5 pM, inhibiting the bioactivity of IL‑5 with in vitro IC50 value of 4 pM by blocking its binding to the alpha chain of the IL‑5 receptor complex expressed on the cell surface. Depemokimab‑ulaa contains a triple amino acid substitution (YTE) in the fragment crystallizable (Fc) region which increases binding to the neonatal Fc receptor and thereby extends the elimination half‑life. These properties support the dosing interval of every 6 months.

IL‑5 is the major cytokine responsible for the growth and differentiation, recruitment, activation, and survival of eosinophils. Inflammation is an important component in the pathogenesis of asthma. Multiple cell types (e.g., mast cells, eosinophils, neutrophils, macrophages, lymphocytes) and mediators (e.g., histamine, eicosanoids, leukotrienes, cytokines) are involved in inflammation. Depemokimab‑ulaa, by inhibiting IL‑5 signaling, reduced the production and survival of eosinophils; however, the mechanism of depemokimab‑ulaa action in asthma has not been definitively established.

12.2 Pharmacodynamics

In placebo‑controlled studies involving adult and pediatric patients aged 12 years and older with asthma, a 100 mg dose of EXDENSUR administered SC every 6 months for 52 weeks reduced blood eosinophils to a geometric mean count of 57 cells/mcL (95% CI: 51, 63) at Week 52. This corresponded to a geometric mean reduction of 79% (95% CI: 75.8, 81.8) compared to placebo. This magnitude of blood eosinophil reduction was observed within 2 weeks of treatment (at the first assessment) and was maintained throughout the treatment period.

12.3 Pharmacokinetics

The pharmacokinetics of depemokimab‑ulaa were approximately dose‑proportional in patients with asthma following SC administration over a dose range of 0.1‑times the recommended dose to 3‑times the recommended dose. After SC administration of 100 mg of EXDENSUR every 6 months in patients with severe asthma, the mean (SD) model-based estimated trough concentration of depemokimab‑ulaa at Week 26 was approximately 1.30 (0.44) mcg/mL. The mean (SD) model-based estimated average steady‑state plasma concentration over a single dosing interval was 6.16 (1.62) mcg/mL.

Absorption

Depemokimab‑ulaa median Tmax was approximately 14 days. There was no accumulation following repeat SC administration once every 6 months.

Distribution

The estimated typical apparent volume of distribution is 6.3 L.

Elimination

The estimated mean (SD) elimination half‑life was 48 (4.7) days following SC administration of EXDENSUR. The estimated typical apparent clearance was 0.092 L/day.

Metabolism: Depemokimab‑ulaa is a monoclonal antibody which is expected to be metabolized into small peptides and amino acids by catabolic pathways.

Specific Populations

No clinically significant differences in the pharmacokinetics of depemokimab‑ulaa were observed based on age (12 to 93 years), sex, race (73% White, 7% Black, 19% Asian), body weight (34.6 to 161 kg), renal impairment (eGFR ≥90 mL/min/1.73 m^2 [normal, N = 548]; eGFR 60 to <90 mL/min/1.73 m^2 [mild, N = 380]; eGFR 30 to <60 mL/min/1.73 m^2 [moderate, N = 31], and eGFR ≤30 mL/min/1.73 m^2 [severe, N = 2]), or baseline hepatic function biomarkers (alanine aminotransferase [ALT; 5 to 153 IU/L], aspartate aminotransferase [AST; 9 to 115 IU/L], and bilirubin [1.7 to 42 micromol/L]).

Pediatric Patients: There are limited pharmacokinetic data available in the pediatric population. The pharmacokinetics of depemokimab‑ulaa in pediatric patients aged 12 to 17 years were consistent with adults. The pharmacokinetics of depemokimab‑ulaa have not been studied in pediatric patients aged less than 12 years.

Drug Interaction Studies

No drug interaction studies have been conducted.

12.6 Immunogenicity

The observed incidence of anti‑drug antibodies is highly dependent on the sensitivity and specificity of the assay. Differences in assay methods preclude meaningful comparisons of the incidence of anti‑drug antibodies (ADA) in the studies described below with the incidence of ADA in other studies, including those of EXDENSUR or of other depemokimab products.

In adults and pediatric patients aged 12 years and older with asthma, the incidence of ADA to depemokimab in patients treated with EXDENSUR 100 mg once every 6 months in SWIFT‑1, SWIFT‑2, and an open‑label extension was 10% (66/691). Among ADA‑positive patients, 6% (4/66) developed neutralizing antibodies.

There was no identified clinically significant effect of ADA on the pharmacokinetics, pharmacodynamics, safety, or efficacy of EXDENSUR.

13 NON-CLINICAL TOXICOLOGY

13.1 Carcinogenesis, Mutagenesis, Impairment of Fertility

No genotoxicity or carcinogenicity studies have been conducted.

Male and female fertility were unaffected based upon no adverse histopathological findings in the reproductive organs from cynomolgus monkeys receiving SC dosages up to 100 mg/kg depemokimab‑ulaa for 6 months. Mating and reproductive performance were unaffected in male and female CD‑1 mice receiving an analogous antibody, which inhibits the activity of murine IL‑5.

14 CLINICAL STUDIES

The efficacy of EXDENSUR for the add‑on maintenance treatment of severe asthma characterized by an eosinophilic phenotype was evaluated in 2 replicate, randomized (2:1 to EXDENSUR or placebo), double‑blind, parallel‑group, placebo‑controlled, multicenter clinical trials (SWIFT‑1 [NCT04719832] and SWIFT‑2 [NCT04718103]) of 52 weeks duration. The trials enrolled adult and pediatric patients aged 12 years and older with asthma characterized by an eosinophilic phenotype, defined as a blood eosinophil count ≥150 cells/mcL at screening or ≥300 cells/mcL documented in the year prior to study entry. Patients were required to have 2 or more asthma exacerbations requiring treatment with systemic corticosteroids (SCS) in the prior year while on background asthma therapy consisting of a medium‑ to high‑dose ICS plus at least one additional asthma controller with or without maintenance oral corticosteroids (OCS). Patients were also required to have reduced lung function at baseline (pre‑bronchodilator forced expiratory volume in 1 second [FEV1] <80% predicted normal in adults; FEV1 <90% or FEV1 to forced vital capacity ratio <0.8 in pediatric patients aged 12 years and older). Patients were enrolled without requiring a minimum baseline Asthma Control Questionnaire‑5 (ACQ‑5) score. In these trials, EXDENSUR 100 mg was administered SC once every 6 months for a total of 2 doses in addition to background asthma therapy. The efficacy population consisted of 762 patients who received at least 1 dose of EXDENSUR 100 mg or placebo in SWIFT‑1 (N = 382) and SWIFT‑2 (N = 380).

The demographics and baseline characteristics of the efficacy population in SWIFT‑1 and SWIFT‑2 are provided in Table 2.

Table 2. Demographics and Baseline Characteristics of Adult and Pediatric Patients Aged 12 Years and Older with Severe Asthma in SWIFT-1 and SWIFT-2
 | SWIFT‑1; N = 382 | SWIFT‑2; N = 380
Age (years), n (%)
12‑17 | 8 (2) | 22 (6)
18‑64 | 276 (72) | 262 (69)
≥65 | 98 (26) | 96 (25)
Mean (SD) | 54 (14.2) | 53 (16.2)
Female, n (%) | 223 (58) | 241 (63)
Race, n (%)
White | 316 (83) | 272 (72)
Asian | 58 (15) | 75 (20)
Black or African American | 8 (2) | 28 (7)
Other | 0 | 5 (1)
Hispanic or Latino, n (%) | 23 (6) | 65 (17)
Never smoked, n (%) | 288 (75) | 294 (77)
Duration of asthma (years), mean (SD) | 22 (16.2) | 25 (18.5)
Pre‑bronchodilator % predicted FEV1, mean (SD) | 62 (15.2) | 62 (15.9)
% reversibility, mean (SD) | 17 (15.3) | 18 (17.4)
Eosinophil count (cells/mcL), median (min; max) | 310; (20; 2,360) | 340; (10; 4,440)
Exacerbations in previous year, mean (SD) | 2.2 (0.7) | 2.7 (1.9)
High‑dose ICS use, n (%)a | 203 (53) | 226 (59)
ICS + LABA + LAMA use, n (%) | 95 (25) | 127 (33)
Maintenance OCS use, n (%) | 21 (5) | 19 (5)
Total IgE (U/mcL),; median (min; max) | 185; (2; 12,142) | 180; (2; 16,199)
FEV1 = forced expiratory volume in 1 second; ICS = inhaled corticosteroid; IgE = immunoglobulin E; LABA = long‑acting beta agonist; LAMA = long‑acting muscarinic antagonist; mcL = microliter; N = number of patients in the efficacy population; n = number of patients in the respective group; OCS = oral corticosteroid; SD = standard deviation; U = units.
a Medium ICS dose = 440 mcg fluticasone propionate (FP) daily or equivalent; High ICS dose >440 mcg FP daily or equivalent.

Exacerbations

The primary efficacy endpoint for SWIFT‑1 and SWIFT‑2 was the annualized rate of clinically significant exacerbations over the 52‑week treatment period. A clinically significant exacerbation was defined as worsening of asthma requiring use of SCS such as intravenous (IV) or oral steroids for at least 3 days or a single intramuscular (IM) corticosteroid dose and/or hospitalization and/or Emergency Department visit. For patients on maintenance SCS, at least double the existing maintenance dose for at least 3 days was required. All patients experiencing an exacerbation were treated with SCS.

In SWIFT‑1 and SWIFT‑2, the annualized rate of asthma exacerbations was significantly lower in patients receiving EXDENSUR compared to placebo (Table 3). During the 52‑week treatment period, fewer patients experienced exacerbations in the EXDENSUR group (32% and 32%) compared to the placebo group (46% and 50%) in SWIFT‑1 and SWIFT‑2, respectively.

Table 3. Annualized Rate of Clinically Significant Asthma Exacerbations Over 52 Weeks in SWIFT-1 and SWIFT-2
 | SWIFT‑1 |  | SWIFT‑2
 | EXDENSUR; N = 250 | Placebo; N = 132 | EXDENSUR; N = 252 | Placebo; N = 128
Annualized rate of clinically significant asthma exacerbations | 0.46 | 1.11 | 0.56 | 1.08
Rate ratio (95% CI) | 0.42 (0.30, 0.59) |  | 0.52 (0.36, 0.73)
P‑value | <0.001 |  | <0.001
N = number of patients in the efficacy population.
Note: Results obtained from a negative binomial model with an offset term for years in study and fixed effects for treatment group, asthma exacerbation history, baseline ICS dose, geographical region, and baseline pre‑bronchodilator % predicted FEV1.

The percentage of patients with exacerbations requiring hospitalization and/or Emergency Department visit was numerically lower for patients treated with EXDENSUR (1% and 4%) compared with placebo (8% and 10%) in SWIFT‑1 and SWIFT‑2, respectively.

In SWIFT‑1 and SWIFT‑2, the time to first clinically significant exacerbation was longer for EXDENSUR compared to placebo (Figures 3 and 4).

Figure 3. Kaplan Meier Curve for Time to First Clinically Significant Exacerbation (SWIFT‑1)

Shaded areas represent 95% confidence intervals.

Figure 4 Kaplan Meier Curve for Time to First Clinically Significant Exacerbation (SWIFT‑2)

Shaded areas represent 95% confidence intervals.

Lung Function

In SWIFT‑1 and SWIFT‑2, the mean change from baseline in pre‑bronchodilator FEV1 for EXDENSUR was 160 mL and 240 mL, respectively, compared to 160 mL and 184 mL for placebo. The treatment difference in SWIFT‑1 and SWIFT‑2 relative to placebo was -1 mL (95% CI: -89, 88) and 56 mL (95% CI: -43, 154), respectively.

Patient-Reported Outcome

In SWIFT‑1 and SWIFT‑2, the proportion of ACQ‑5 responders (clinically meaningful improvement defined as a decrease in score of 0.5 or more) at Week 52 was 54% for EXDENSUR in both studies compared to 55% and 53%, respectively, for placebo.

16 HOW SUPPLIED/STORAGE AND HANDLING

How Supplied

EXDENSUR (depemokimab‑ulaa) injection is a sterile, preservative‑free, colorless, yellow to brown, clear to opalescent solution for subcutaneous (SC) use. The pens and syringes are not made with natural rubber latex. EXDENSUR injection is supplied as described in Table 4.

Table 4. EXDENSUR Injection Package Configuration
Package Configuration | Strength | NDC
1 single‑dose, prefilled pen with attached 29‑gauge, half‑inch needle in a carton | 100 mg/mL | 0173‑0927‑31
1 single‑dose, prefilled syringe with attached 29‑gauge, half‑inch needle with needle guard in a carton | 100 mg/mL | 0173‑0927‑42

Storage and Handling

Store refrigerated at 36°F to 46°F (2°C to 8°C) in the original carton to protect from light.

Do not freeze. Do not shake. Avoid exposure to heat.

The prefilled pen and prefilled syringe can be removed from the refrigerator and kept in the unopened carton, protected from light for up to 7 days at room temperature up to 86°F (30°C). Discard if left out of the refrigerator for more than 7 days.

The prefilled pen or prefilled syringe must be administered within 8 hours once removed from the carton. Discard if not administered within 8 hours.

17 PATIENT COUNSELING INFORMATION

Advise the patient to read the FDA‑approved patient labeling (Patient Information).

Hypersensitivity Reactions

Inform patients of hypersensitivity reactions, including anaphylaxis, that can occur following administration of EXDENSUR. Instruct patients to contact their healthcare provider if they experience symptoms of a hypersensitivity reaction [see Warnings and Precautions (5.1)].

Acute Asthma Symptoms or Deteriorating Disease

Inform patients that EXDENSUR does not treat acute asthma symptoms or acute exacerbations. Advise patients to seek medical advice if their asthma remains uncontrolled or worsens after initiation of treatment with EXDENSUR [see Warnings and Precautions (5.2)].

Risk Associated with Abrupt Reduction of Corticosteroid Dosage

Advise patients to not abruptly discontinue systemic or inhaled corticosteroids after initiation of EXDENSUR therapy. Inform patients that reduction in corticosteroid dose may be associated with systemic withdrawal symptoms and/or unmask conditions previously suppressed by systemic corticosteroid therapy. Inform patients that reductions in corticosteroid dose, if appropriate, should be gradual and performed under the supervision of a healthcare provider [see Warnings and Precautions (5.3)].

EXDENSUR Exposure to Fetus or Infants During Pregnancy

Advise patients that the potential clinical impact of prolonged and increased EXDENSUR exposure in infants that were exposed in utero is unknown. Inform providers of infants exposed to EXDENSUR in utero of the potential for the infant to be exposed to elevated levels of EXDENSUR for a prolonged period [see Use in Specific Populations (8.1)].

Advise patients who are exposed to EXDENSUR during pregnancy to contact GlaxoSmithKline at 1‑888‑825‑5249.

Trademarks are owned by or licensed to the GSK group of companies.

Manufactured by
GlaxoSmithKline LLC
2929 Walnut Street, Suite 1700
Philadelphia, PA 19104
U.S. License No. 1727

Distributed by
GlaxoSmithKline
Durham, NC 27701

©2025 GSK group of companies or its licensor.

EXD:1PI

PATIENT INFORMATION

EXDENSUR [Ex‑DEN‑shur]

(depemokimab‑ulaa)

injection, for subcutaneous use

What is EXDENSUR?

- EXDENSUR is a prescription medicine:
  - for the add‑on maintenance treatment of severe asthma in people 12 years and older whose asthma is not controlled with their current medicines.
  - EXDENSUR helps prevent severe asthma attacks (exacerbations).
  - EXDENSUR is not used to treat sudden breathing problems that occur with asthma. Tell your healthcare provider if your asthma does not get better or if it gets worse after you start treatment with EXDENSUR.
- EXDENSUR works by targeting inflammation that plays a major role in severe asthma. EXDENSUR reduces blood eosinophils. Eosinophils are a type of white blood cells that may contribute to your disease.

It is not known if EXDENSUR is safe and effective in children with asthma under 12 years of age.

Before using EXDENSUR, tell your healthcare provider about all of your medical conditions, including if you:

- are taking systemic or inhaled corticosteroid medicines. Do not change or stop taking your corticosteroid medicines unless instructed by your healthcare provider. This may cause other symptoms that were controlled by the corticosteroid medicine to come back.
- have a parasitic (helminth) infection.
- are pregnant or plan to become pregnant. Babies exposed to EXDENSUR before birth may have higher and longer‑lasting levels of the medicine in their bodies. It is not known if EXDENSUR may harm your unborn baby. If you become pregnant while taking EXDENSUR contact GlaxoSmithKline at 1‑888‑825‑5249.
- are breastfeeding or plan to breastfeed. You and your healthcare provider should decide if you will use EXDENSUR and breastfeed. You should not do both without talking with your healthcare provider first.
- Tell your healthcare provider about all the medicines you take, including prescription and over‑the‑counter medicines, vitamins, and herbal supplements.
- Do not change or stop taking your other medicines unless instructed to do so by your healthcare provider.

How EXDENSUR is given:

A healthcare provider will inject EXDENSUR under your skin (subcutaneously) every 6 months. If you miss a dose of EXDENSUR, contact your healthcare provider to get your next dose as soon as you can.

What are the possible side effects of EXDENSUR?

EXDENSUR can cause serious side effects including:

- allergic (hypersensitivity) reactions, including anaphylaxis. Serious allergic reactions can happen after you get your EXDENSUR injection. Contact your healthcare provider or get emergency help right away if you have any of the following symptoms of an allergic reaction:

- swelling of your face, mouth, and tongue
- fainting, dizziness, feeling lightheaded (low blood pressure)
- hives

- breathing problems
- rash

The most common side effects of EXDENSUR include:

- upper respiratory tract infection (common cold, sinus infection)
- sneezing, nasal congestion, runny nose, and nasal itching (allergic rhinitis)
- flu or flu‑like symptoms
- joint pain
- sore throat (pharyngitis)

These are not all of the possible side effects of EXDENSUR.

Call your doctor for medical advice about side effects. You may report side effects to FDA at 1‑800‑FDA‑1088.

General information about the safe and effective use of EXDENSUR.

Medicines are sometimes prescribed for purposes other than those listed in a Patient Information leaflet.

You can ask your pharmacist or healthcare provider for information about EXDENSUR that is written for health professionals.

What are the ingredients in EXDENSUR?

Active ingredients: depemokimab‑ulaa

Inactive ingredients: arginine HCl, edetate disodium, histidine, L‑histidine HCl monohydrate, polysorbate 80, trehalose, Water for Injection.

For more information about EXDENSUR, call 1‑833‑EXDENSUR or visit our website at EXDENSUR.com.

Trademarks are owned by or licensed to the GSK group of companies.

Manufactured by:

GlaxoSmithKline LLC, Philadelphia, PA 19104, U.S. License No. 1727

Distributed by:

GlaxoSmithKline, Durham, NC 27701

©2025 GSK group of companies or its licensor.

EXD:1PIL

This Patient Information has been approved by the U.S. Food and Drug Administration Issued: December 2025

PACKAGE/LABEL PRINCIPAL DISPLAY PANEL

PRINCIPAL DISPLAY PANEL

NDC 0173-0927-42

EXDENSUR

(depemokimab-ulaa)

Injection

Rx Only

GSK

100 mg/mL

For subcutaneous use

Prefilled Syringe

Contents:

- 1 Single-Dose 1-mL Prefilled Syringe

- Prescribing Information

- Patient Information

©2025 GSK group of companies or its licensor.

Rev. 12/25

62000000099386